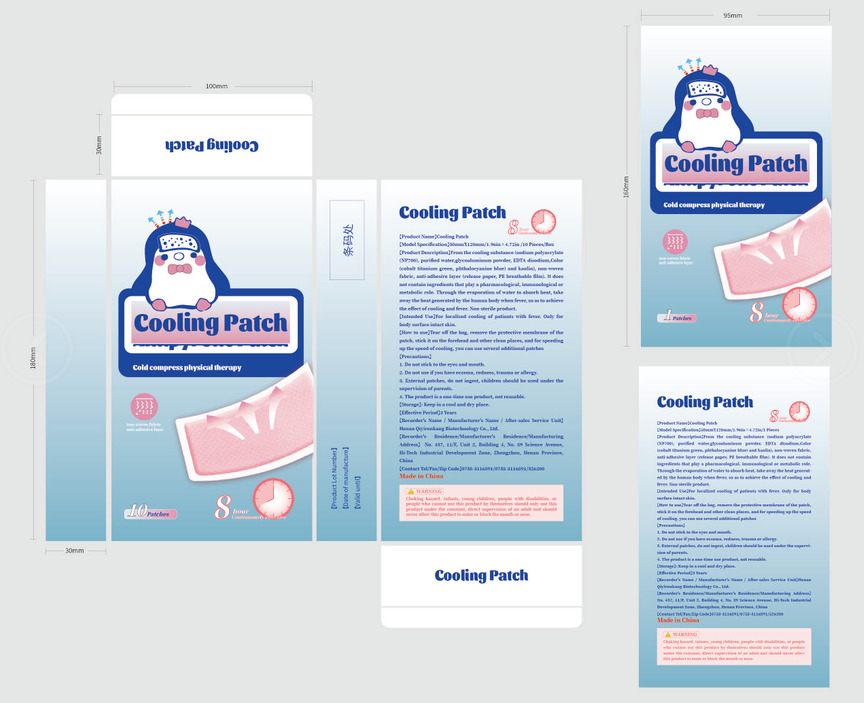 DRUG LABEL: Cooling Patch
NDC: 84776-001 | Form: GEL
Manufacturer: Henan Qiyirenkang Biotechnology Co., Ltd.
Category: otc | Type: HUMAN OTC DRUG LABEL
Date: 20241016

ACTIVE INGREDIENTS: MENTHOL 0.01 g/100 g; GLYCERIN 23 g/100 g; WATER 66.19 g/100 g; BORNEOL 0.2 g/100 g
INACTIVE INGREDIENTS: EDETATE DISODIUM; CARBOXYMETHYLCELLULOSE SODIUM; TARTARIC ACID; SODIUM POLYACRYLATE (2500000 MW); FD&C BLUE NO. 1; DMDM HYDANTOIN; POLYETHYLENE GLYCOL 400; POVIDONE K90

84776-001

Active Ingredient(s)

H2O 66.19%

GLYCERIN 23%

2-BORNEOL 0.2%

Menthol 0.01%

Purpose

Antipyretic

Use

For localized cooling of patients with fever. Only for body surface intact skin.

Warnings

1. Do not stick to the eyes and mouth.
2. Do not use if you have eczema, redness, trauma or allergy.
3. External patches, do not ingest, children should be used under the supervision of parents.
4. The product is a one-time use product, not reusable.

Do not use

Children should use it under parental supervision

WHEN USING

Tear off the bag, remove the protective membrane of the patch, stick it on the forehead and other clean places, and for speeding up the speed of cooling, you can use several additional patches

Keep out of reach of children. If swallowed, get medical help or contact a Poison Control Center right away.

Directions

Tear off the bag, remove the protective membrane of the patch, stick it on the forehead and other clean places, and for speeding up the speed of cooling, you can use several additional patches

Inactive ingredients

SODIUM POLYACRYLAT

CARBOXYMETHYLCELLULOSE SODIUM CMC

DMDM HYDANTOIN

POLYETHYLENE GLYCOL 400

EDETATE DISODIUM

TARTARIC ACID

20% POVIDONE K90

1%FD&C BLUE NO. 1